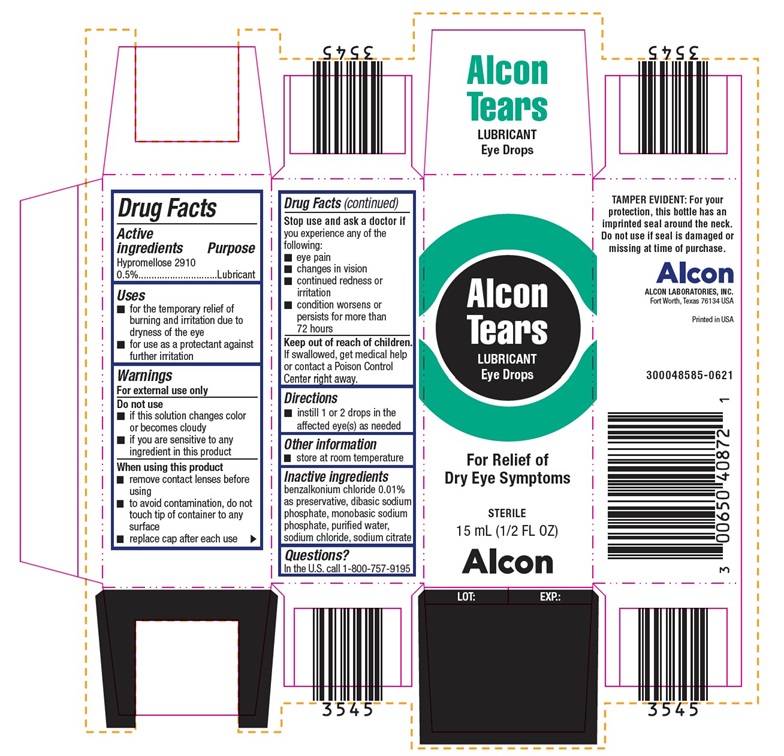 DRUG LABEL: Alcon Tears Lubricant Eye Drops
NDC: 0065-0408 | Form: SOLUTION/ DROPS
Manufacturer: Alcon Laboratories, Inc.
Category: otc | Type: HUMAN OTC DRUG LABEL
Date: 20231214

ACTIVE INGREDIENTS: Hypromellose 2910 (4000 Mpa.S) 5 mg/1 mL
INACTIVE INGREDIENTS: Benzalkonium Chloride; Sodium Phosphate, Dibasic, Unspecified Form; Sodium Phosphate, Monobasic, Unspecified Form; Water; Sodium Chloride; Sodium Citrate, Unspecified Form

Drug Facts

ACTIVE INGREDIENT

Active ingredients | Purpose
Hypromellose 2910 0.5% | Lubricant

Uses

- for the temporary relief of burning and irritation due to dryness of the eye
- for use as a protectant against further irritation

Warnings

For external use only

Do not use

- if this solution changes color or becomes cloudy
- if you are sensitive to any ingredient in this product

When using this product

- remove contact lenses before using
- to avoid contamination, do not touch tip of container to any surface
- replace cap after each use

Stop use and ask a doctor if

you experience any of the following:

- eye pain
- changes in vision
- continued redness or irritation
- condition worsens or persists for more than 72 hours

Keep out of reach of children.

If swallowed, get medical help or contact a Poison Control Center right away.

Directions

- instill 1 or 2 drops in the affected eye(s) as needed

Other information

- store at room temperature

Inactive ingredients

benzalkonium chloride 0.01% as preservative, dibasic sodium phosphate, monobasic sodium phosphate, purified water, sodium chloride, sodium citrate

Questions?

In the U.S. call 1-800-757-9195

PRINCIPAL DISPLAY PANEL

Alcon Tears
LUBRICANT
Eye Drops
For Relief of Dry Eye Symptoms
STERILE
15 mL (1/2 FL OZ)
Alcon
TAMPER EVIDENT: For your protection, this bottle has an imprinted seal around the neck.
Do not use if seal is damaged or missing at time of purchase.
Alcon
ALCON LABORATORIES, INC.
Fort Worth, Texas 76134 USA
Printed in USA